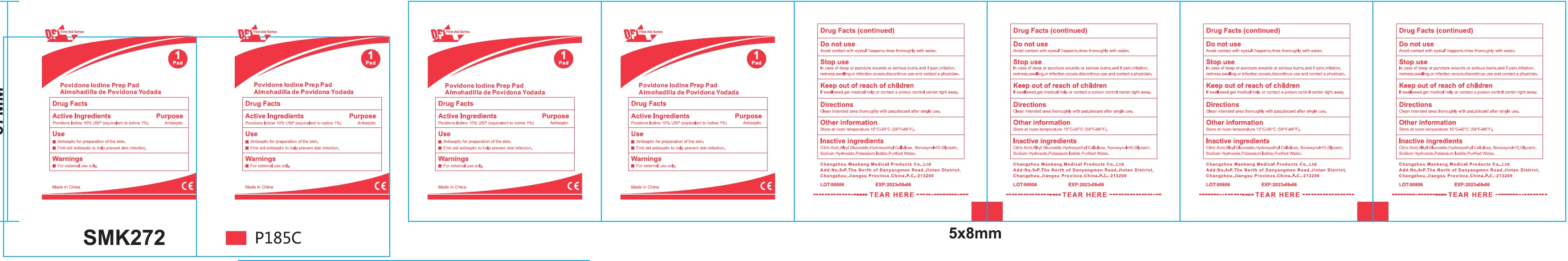 DRUG LABEL: OP First Aid Series Povidone Iodine Prep Pad
NDC: 72459-012 | Form: CLOTH
Manufacturer: Yiwu Ori-Power Medtech Co.,Ltd.
Category: otc | Type: HUMAN OTC DRUG LABEL
Date: 20260101

ACTIVE INGREDIENTS: POVIDONE-IODINE 100 mg/1 mL
INACTIVE INGREDIENTS: CITRIC ACID MONOHYDRATE; HYDROXYETHYL CELLULOSE, UNSPECIFIED; NONOXYNOL-10; GLYCERIN; SODIUM HYDROXIDE; POTASSIUM IODIDE; WATER

OP First Aid Series Povidone Iodine Prep Pad

Active Ingredients

Povidone Iodine 10% USP (equivalent to iodine 1%)

Purpose

Antiseptic

Use

- Antiseptic for preparation of the skin.
- First aid antiseptic to help prevent skin infection.

Warnings

For external use only.

Do not use

Avoid contact with eyes.If happens,rinse thoroughly with water.

Stop use

In case of deep or puncture wounds or serious burns,and if pain,irritation, redness, swelling,or infection occurs,discontinue use and contact a physician.

Keep out of reach of children

If swallowed, get medical help or contact a poison control center right away.

Directions

Clean intended area thoroughly with pad.discard after single use.

Other information

Store at room temperature 15°C-30°C (59°F-86°F).

Inactive ingredients

Citric Acid, Alkyl Glucoside,Hydroxyethyl Cellulose, Nonoxynol-10, Glycerin, Sodium Hydroxide, Potassium Iodide, Purified Water.